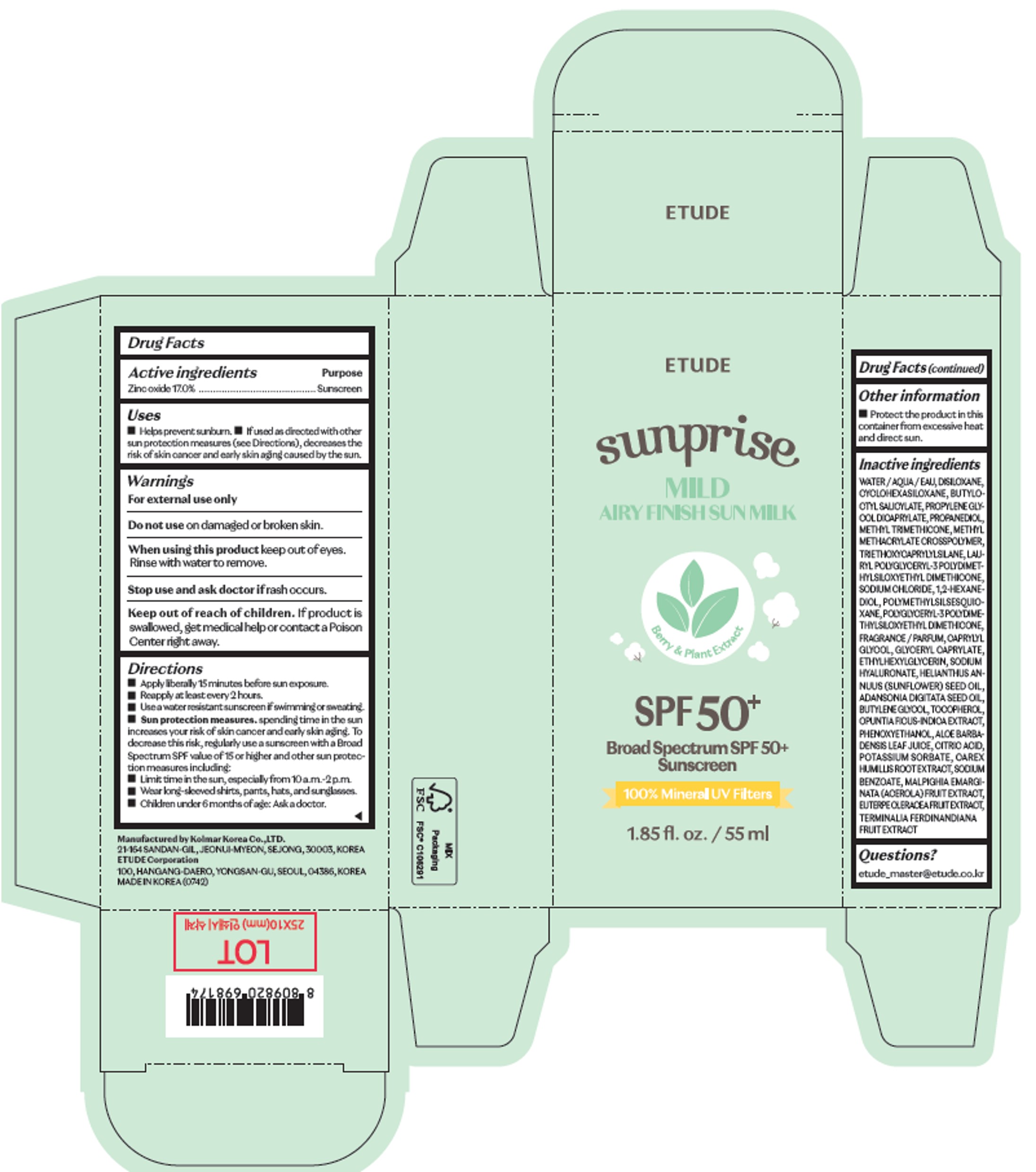 DRUG LABEL: ETUDE Sun-Prise Mild Airy Finish
NDC: 84468-742 | Form: CREAM
Manufacturer: ETUDE CORPORATION
Category: otc | Type: HUMAN OTC DRUG LABEL
Date: 20240908

ACTIVE INGREDIENTS: ZINC OXIDE 17 g/100 mL
INACTIVE INGREDIENTS: 1,2-HEXANEDIOL; WATER; PROPANEDIOL

Route of Administration

TOPICAL

Warnings

For external use only. Do not use on damaged or broken skin. When using this product keep out of eyes. Rinse with water to remove. Stop use and ask doctor if rash occurs. Keep out of reach of children. If product is swallowed, get me dical help or contact a Poison Center right away.

Other Ingredients

WATER / AQUA / EAU, DISILOXANE, CYCLOHEXASILOXANE, BUTYLO CTYL SALICYLATE, PROPYLENE GLY COL DICAPRYLATE, PROPANEDIOL, METHYL TRIMETHICONE, METHYL METHACRYLATE CROSSPOLYMER, TRIETHOXYCAPRYLYLSILANE, LAU RYL POLYGLYCERYL-3 POLYDIMET HYLSILOXYETHYL DIMETHICONE, SODIUM CHLORIDE, 1,2-HEXANE DIOL, POLYMETHYLSILSESQUIO XANE, POLYGLYCERYL-3 POLYDIME THYLSILOXYETHYL DIMETHICONE, FRAGRANCE / PARFUM, CAPRYLYL GLYCOL, GLYCERYL CAPRYLATE, ETHYLHEXYLGLYCERIN, SODIUM HYALURONATE, HELIANTHUS AN NUUS (SUNFLOWER) SEED OIL, ADANSONIA DIGITATA SEED OIL, BUTYLENE GLYCOL, TOCOPHEROL, OPUNTIA FICUS-INDICA EXTRACT, PHENOXYETHANOL, ALOE BARBA DENSIS LEAF JUICE, CITRIC ACID, POTASSIUM SORBATE, CAREX HUMILLIS ROOT EXTRACT, SODIUM BENZOATE, MALPIGHIA EMARGI NATA (ACEROLA) FRUIT EXTRACT, EUTERPE OLERACEA FRUIT EXTRACT, TERMINALIA FERDINANDIANA FRUIT EXTRACT

Uses

◼ Helps prevent sunburn. ◼ If used as directed with other sun protection measures (see Directions), decreases the risk of skin cancer and early skin aging caused by the sun.

Purpose

Sunscreen